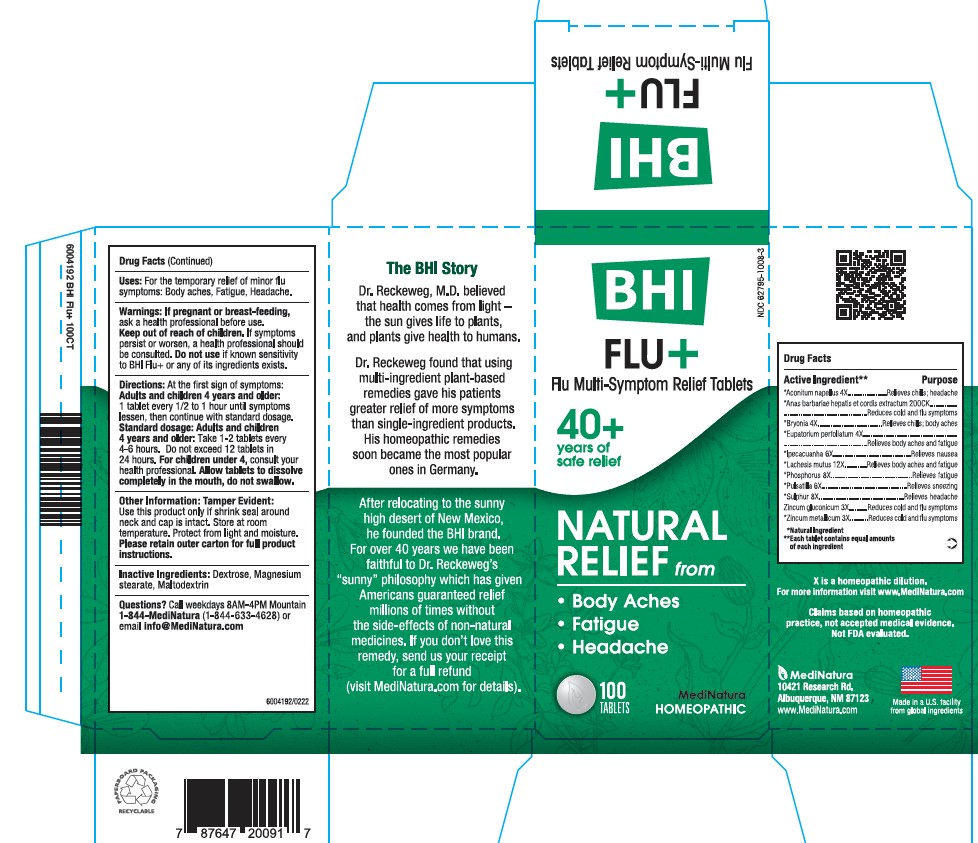 DRUG LABEL: BHI Flu Plus
NDC: 62795-1008 | Form: TABLET
Manufacturer: MediNatura Inc
Category: homeopathic | Type: HUMAN OTC DRUG LABEL
Date: 20230413

ACTIVE INGREDIENTS: ACONITUM NAPELLUS 4 [hp_X]/1 1; CAIRINA MOSCHATA HEART/LIVER AUTOLYSATE 200 [hp_C]/1 1; BRYONIA ALBA WHOLE 4 [hp_X]/1 1; EUPATORIUM PERFOLIATUM FLOWERING TOP 4 [hp_X]/1 1; IPECAC 6 [hp_X]/1 1; LACHESIS MUTA VENOM 12 [hp_X]/1 1; PHOSPHORUS 8 [hp_X]/1 1; PULSATILLA VULGARIS 6 [hp_X]/1 1; SULFUR 8 [hp_X]/1 1; ZINC GLUCONATE 3 [hp_X]/1 1; ZINC 3 [hp_X]/1 1
INACTIVE INGREDIENTS: MAGNESIUM STEARATE; MALTODEXTRIN; DEXTROSE

BHI Flu + Tablet

ACTIVE INGREDIENTS

Each tablet contains: *Aconitum napellus 4X, *Anas barbariae, hepatis et cordis extractum 200 CK, *Bryonia alba 4X, *Eupatorium perfoliatum 4X, *Ipecacuanha 6X, *Lachesis mutus 12X, *Phosphorus 8X, *Pulsatilla 6X, *Sulphur 8X, Zincum gluconicum 3X, Zincum metallicum 3X 27.3 mg each.

*Natural Ingredients

INACTIVE INGREDIENTS

Inactive Ingredients: Dextrose, Magnesium Stearate, Maltodextrin

PURPOSE

Relieves Flu Symptoms:

• Body Aches

• Fatigue

• Headache

USES

For the temporary relief of minor body aches, fatigue, headache

DIRECTIONS

At first sign of symptoms:

Adults and children 4 years and older:

1 tablet every 1/2 to 1 hour until symptoms lessen, then continue with standard dosage.

Standard dosage:

Adults and children 4 years andolder:

Take 1-2 tablets every 4 to 6 hours. Do not exceed 12 tablets in 24 hours.

For children under 4, consult your health professional.

Allow tablets to dissolve completely in the mouth, do not swallow.

WARNINGS

If pregnant or breast-feeding, ask a healthprofessional before use. Keep out of reach of children. If symptoms persist or worsen, a health professional should beconsulted. Do not use if known sensitivity to BHI Flu+ or any of its ingredients exists

KEEP OUT OF REACH OF CHILDREN

PACKAGE LABEL

Add image transcription here...